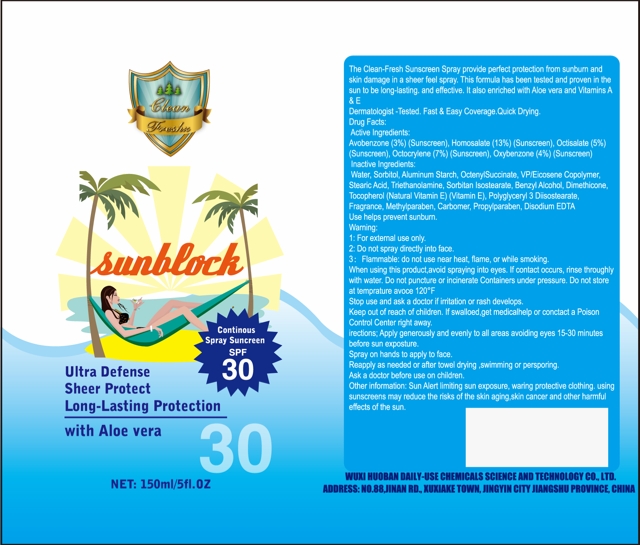 DRUG LABEL: Clean Fresh Sunblock Sunscreen SPF 30 Continuous
NDC: 71712-001 | Form: SPRAY
Manufacturer: Wuxi Huoban Daily-use Chemical Science and Technology Co., Ltd.
Category: otc | Type: HUMAN OTC DRUG LABEL
Date: 20170829

ACTIVE INGREDIENTS: AVOBENZONE 3 g/100 mL; HOMOSALATE 13 g/100 mL; OCTISALATE 5 g/100 mL; OCTOCRYLENE 7 g/100 mL; OXYBENZONE 4 g/100 mL
INACTIVE INGREDIENTS: WATER; SORBITOL; ALUMINUM STARCH OCTENYLSUCCINATE; STEARIC ACID; SORBITAN ISOSTEARATE; BENZYL ALCOHOL; DIMETHICONE; TOCOPHEROL; POLYGLYCERYL-3 DIISOSTEARATE; METHYLPARABEN; CARBOMER COPOLYMER TYPE A; PROPYLPARABEN; DISODIUM HEDTA

Drug Fact

Active Ingredient:

Avobenzone: 3%

Homosalate: 13%

Octisalate: 5%

Octocrylene: 7%

Oxybenzone: 4%

Purpose:

Sunscreen

Uses:

Helps prevent sunburn

Warning:

For external use only

Do not spray directly into face

Flammable. Do not use near heat, flame, or while smoking

When using this product, avoid spray into eyes. If contact occurs, rinse thoroughyl with water. Do not puncture or incinerate container under pressure. Do not store at temperature above 120F

Stop Use and Ask a Doctor if irritation or rash develops

Keep Out of Reach of Children. If swallowed, get medical help or contact a Poison Control Center immediately

Directions:

Apply generously and evenly to all areas avoiding eyes 15-30 minutes before sun exposure.

Spray to hands to apply on face

Reapply as needed or after towel drying, swimming, or persporing

Ask a doctor before use on children

Other Information: Sun Alert: Limit sun exposure, wearing protective clothing, using sunscreens may reduce the risks of skin aging, skin cancer, and other harmful effects of sun

Inactive Ingredient:

Water, Sorbitol, Aluminum Starch Octenyl Succinate, VP/Eicosene Copolymer, Stearic Acid, Triethanolamine, Sorbitan Isostearate, Benzyl Alcohol, Dimethicone, Tocopherol (Natural Vitamin E), Polyglyceryl-3-Diisostearate, Fragrance, Methylparaben, Carbomer, Propylparaben, Disodium EDTA